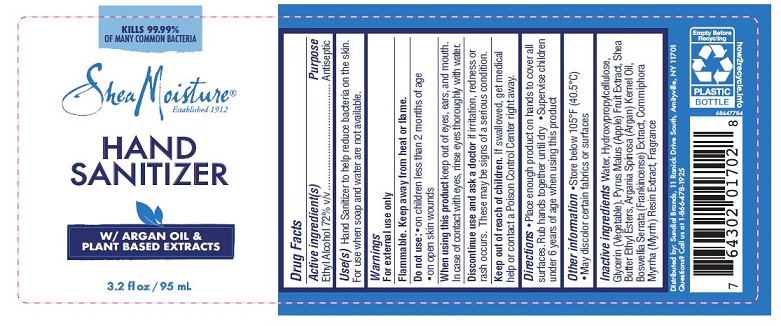 DRUG LABEL: HAND SANITIZER
NDC: 64942-1743 | Form: SOLUTION
Manufacturer: Conopco, Inc. d/b/a/ Unilever
Category: otc | Type: HUMAN OTC DRUG LABEL
Date: 20210506

ACTIVE INGREDIENTS: Alcohol 72 mL/100 mL
INACTIVE INGREDIENTS: Water; Hydroxypropyl Cellulose, Unspecified; Glycerin; Apple; Shea Butter; Argan Oil; Indian Frankincense; Myrrh

Drug Facts

ACTIVE INGREDIENT

Active ingredient(s) | Purpose
Ethyl Alcohol 72% v/v | Antiseptic

INDICATIONS AND USAGE

Use(s) Hand Sanitizer to help reduce bacteria on the skin. For use when soap and water are not available.

Warnings

For external use only
Flammable. Keep away from heat or flame.

Do not use:

- on children less than 2 months of age
- on open skin wounds

When using this product keep out of eyes, ears, and mouth. In case of contact with eyes, rinse eyes thoroughly with water.

ASK DOCTOR

Discontinue use and ask a doctor if irritation, redness or rash occurs. These may be signs of a serious condition.

Keep out of reach of children. If swallowed, get medical help or contact a Poison Control Center right away.

Directions

- Place enough product on hands to cover all surfaces. Rub hands together until dry
- Supervise children under 6 years of age when using this product

Other information

- Store below 105°F (40.5°C)
- May discolor certain fabrics or surfaces

Inactive ingredients

Water, Hydroxypropylcellulose, Glycerin (Vegetable), Pyrus Malus (Apple) Fruit Extract, Shea Butter Ethyl Esters, Argania Spinosa (Argan) Kernel Oil, Boswellia Serrata (Frankincense) Extract, Commiphora Myrrha (Myrrh) Resin Extract, Fragrance

PACKAGE LABEL

KILLS 99.99%
OF MANY COMMON BACTERIA
Shea Moisture®
Established 1912
HAND
SANITIZER
W/ ARGAN OIL &
PLANT BASED EXTRACTS
3.2 fl oz / 95 mL
Distributed by: Sundial Brands, 11 Ranick Drive South, Amityville, NY 11701
Questions? Call us at 1-866-478-1925
Empty Before
Recycling
PLASTIC
BOTTLE
how2recyle.info
68647784